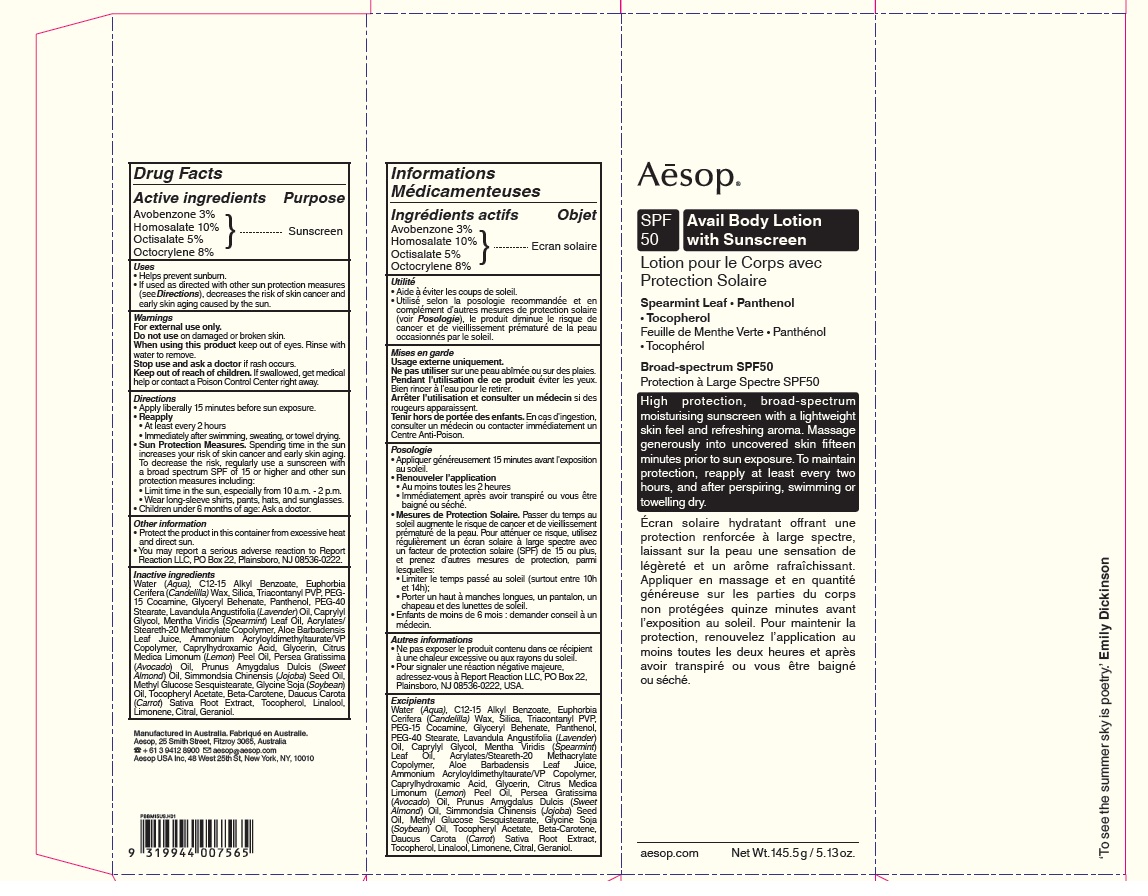 DRUG LABEL: Avail Body with Sunscreen
NDC: 76293-015 | Form: LOTION
Manufacturer: Emeis Cosmetics Pty Ltd
Category: otc | Type: HUMAN OTC DRUG LABEL
Date: 20251217

ACTIVE INGREDIENTS: HOMOSALATE 3500 mg/35 g; OCTOCRYLENE 2800 mg/35 g; OCTISALATE 1750 mg/35 g; AVOBENZONE 1050 mg/35 g
INACTIVE INGREDIENTS: LINALOOL, (+/-)-; LIMONENE, (+)-; CITRAL; GERANIOL; CANDELILLA WAX; WATER; ALKYL (C12-15) BENZOATE; TRICONTANYL POVIDONE; SILICON DIOXIDE; PEG-15 COCAMINE; ETHYL ACRYLATE/METHACRYLIC ACID/STEARETH-20 METHACRYLATE COPOLYMER; PEG-40 STEARATE; GLYCERYL MONOBEHENATE; PANTHENOL; LAVENDER OIL; CAPRYLYL GLYCOL; SPEARMINT OIL; ALOE VERA LEAF; AMMONIUM ACRYLOYLDIMETHYLTAURATE/VP COPOLYMER; CAPRYLHYDROXAMIC ACID; GLYCERIN; LEMON OIL; AVOCADO OIL; ALMOND OIL; JOJOBA OIL; SOYBEAN OIL; .BETA.-CAROTENE; METHYL GLUCOSE SESQUISTEARATE; .ALPHA.-TOCOPHEROL ACETATE, D-; CARROT; TOCOPHEROL

Avail Body Lotion with Sunscreen

Drug Facts

Active ingredients

Avobenzone 3%
Homosalate 10%
Octisalate 5%
Octocrylene 8%

Purpose

Sunscreen

Uses

- Helps prevent sunburn.
- If used as directed with other sun protection measures (see Directions), decreases the risk of skin cancer and early skin aging caused by the sun.

Warnings

For external use only.

Do not use on damaged or broken skin.

When using this product keep out of eyes. Rinse with water to remove.

Keep out of reach of children. If swallowed, get medical help or contact a Poison Control Center right away.

Directions

- Apply liberally 15 minutes before sun exposure.
- Reapply
- At least every 2 hours
- Immediately after swimming, sweating, or towel drying.
- Sun Protection Measures. Spending time in the sun increases your risk of skin cancer and early skin aging. To decrease the risk, regularly use a sunscreen with a broad spectrum SPF of 15 or higher and other sun protection measures including:
  - Limit time in the sun, especially from 10 a.m. - 2 p.m.
  - Wear long-sleeve shirts, pants, hats, and sunglasses.
- Children under 6 months of age: Ask a doctor.

Other information

- Protect the product in this container from excessive heat and direct sun.
- You may report a serious adverse reaction to Report Reaction LLC, PO Box 22, Plainsboro, NJ 08536-0222.

Inactive ingredients

Water (Aqua), C12-15 Alkyl Benzoate, Euphorbia Cerifera (Candelilla) Wax, Silica, Triacontanyl PVP, PEG-15 Cocamine, Glyceryl Behenate, Panthenol, PEG-40 Stearate, Lavandula Angustifolia (Lavender) Oil, Caprylyl Glycol, Mentha Viridis (Spearmint) Leaf Oil, Acrylates/Steareth-20 Methacrylate Copolymer, Aloe Barbadensis Leaf Juice, Ammonium Acryloyldimethyltaurate/VP Copolymer, Caprylhydroxamic Acid, Glycerin, Citrus Medica Limonum (Lemon) Peel Oil, Persea Gratissima (Avocado) Oil, Prunus Amygdalus Dulcis (Sweet Almond) Oil, Simmondsia Chinensis (Jojoba) Seed Oil, Methyl Glucose Sesquistearate, Glycine Soja (Soybean) Oil, Tocopheryl Acetate, Beta-Carotene, Daucus Carota (Carrot) Sativa Root Extract, Tocopherol, Linalool, Limonene, Citral, Geraniol.

Product Packaging

Aēsop ®

SPF
50
Avail Body Lotion
with Sunscreen

Spearmint Leaf • Panthenol • Tocopherol

Broad-spectrum SPF50

High protection, Broad-spectrum moisturising sunscreen with a lightweight skin feel and refreshing aroma.

Massage generously into uncovered skin fifteen minutes prior to sun exposure.

To maintain protection, reapply at least every two hours, and after perspiring, swimming or towelling dry.

www.aesop.com
Net Wt. 145.5 g / 5.13 oz.